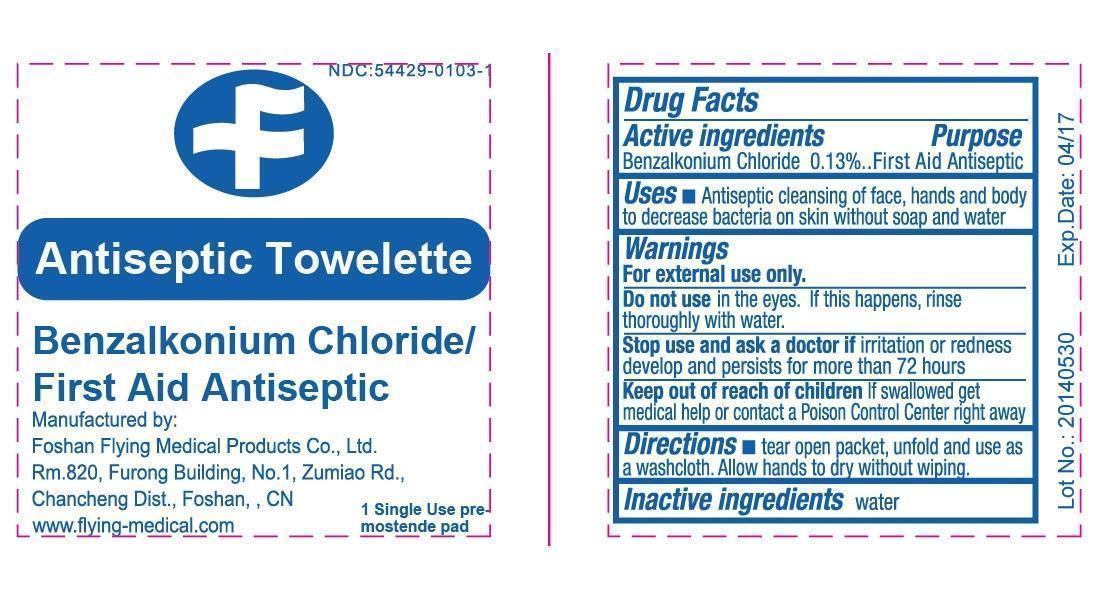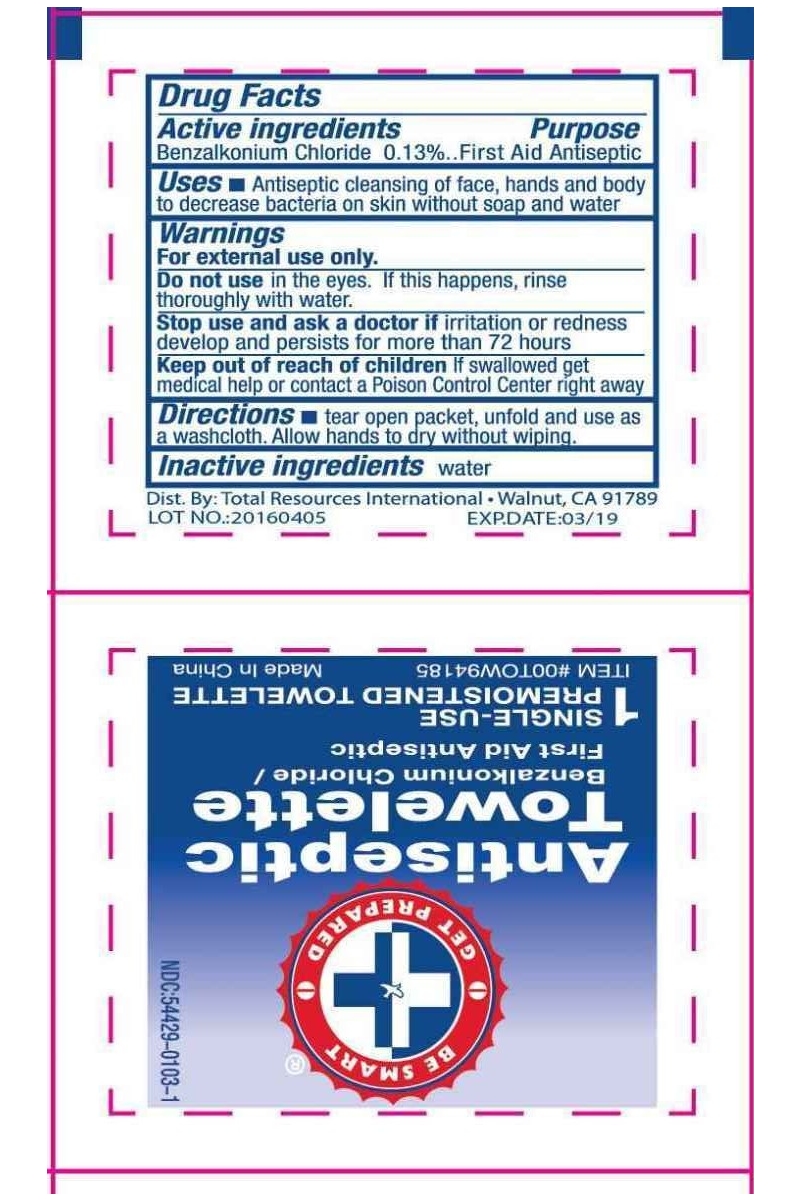 DRUG LABEL: BZK antiseptic swab
NDC: 54429-0103 | Form: SWAB
Manufacturer: Foshan Flying Medical Products Co., Ltd.
Category: otc | Type: HUMAN OTC DRUG LABEL
Date: 20160522

ACTIVE INGREDIENTS: BENZALKONIUM CHLORIDE 1.3 mg/1 mL
INACTIVE INGREDIENTS: WATER

BZK antiseptic swab

INACTIVE INGREDIENTS

Water

DIRECTIONS

Tear open packet, unfold and use as a washcloth. Allow hands to dry without wiping.

WARNINGS

For external use only.
DO NOT USE, in the eyes. If this happens, rinse thoroughly with water.
STOP USE and ASK A DOCTOR: If irritation or redness develop and persists for more than 72 hours.
CAUTION: Keep out of reach of children
If swallowed, get medical help or contact a Poison Control Center right away.

USES

Antiseptic cleansing of face, hands and body to decrease bacteria on skin without soap and water.

CAUTION: Keep out of reach of children

If swallowed, get medical help or contact a Poison Control Center right away.

PURPOSE

First Aid Antiseptic

ACTIVE INGREDIENT

Benzalkonium chloride 0.13%

Drug Facts

ACTIVE INGREDIENT
Benzalkonium chloride 0.13% PURPOSE
First Aid Antiseptic USES
Antiseptic cleansing of face, hands and body to decrease bacteria on skin without soap and water. WARNINGS
For external use only.
DO NOT USE, in the eyes. If this happens, rinse thoroughly with water.
STOP USE and ASK A DOCTOR: If irritation or redness develop and persists for more than 72 hours.
CAUTION: Keep out of reach of children
If swallowed, get medical help or contact a Poison Control Center right away. DIRECTIONS
Tear open packet, unfold and use as a washcloth. Allow hands to dry without wiping. OTHER INFORMATION
Store at room temperature. INACTIVE INGREDIENTS
Water.